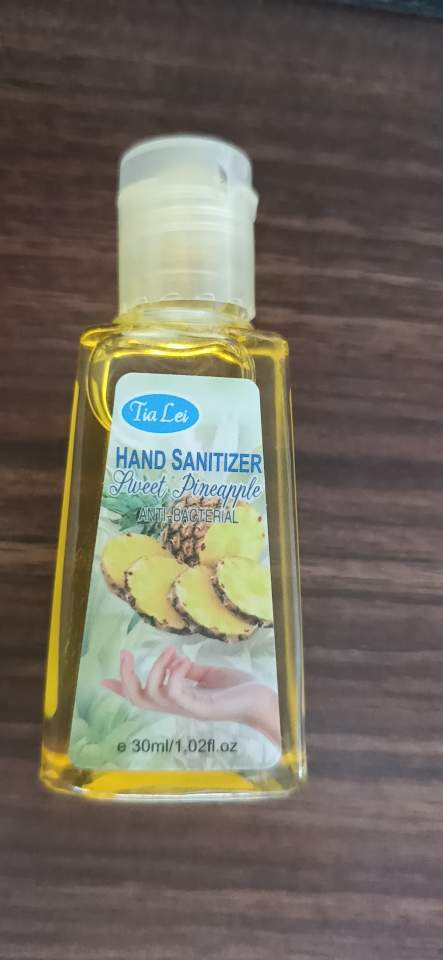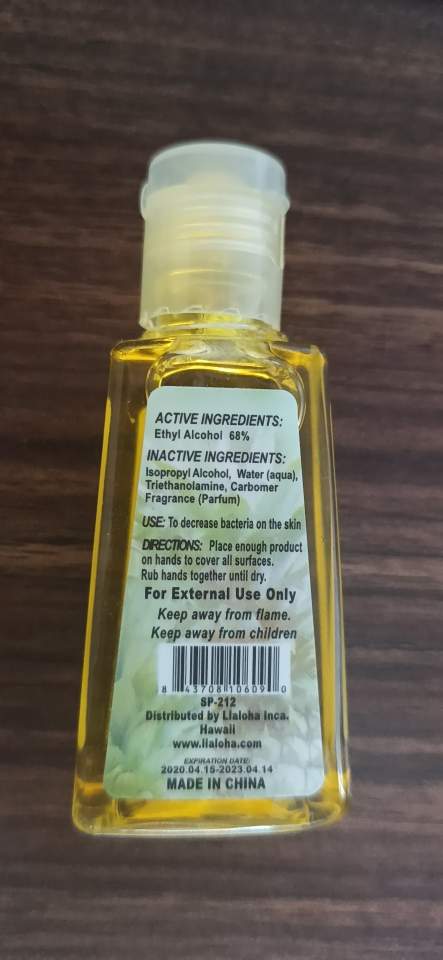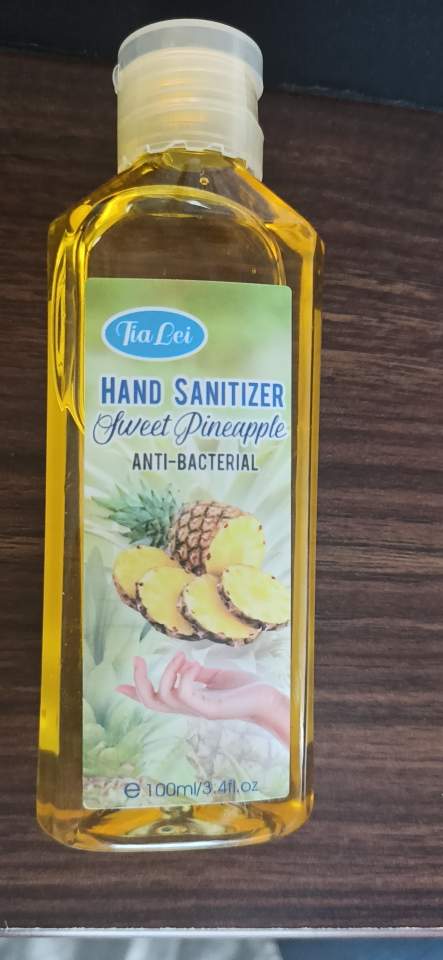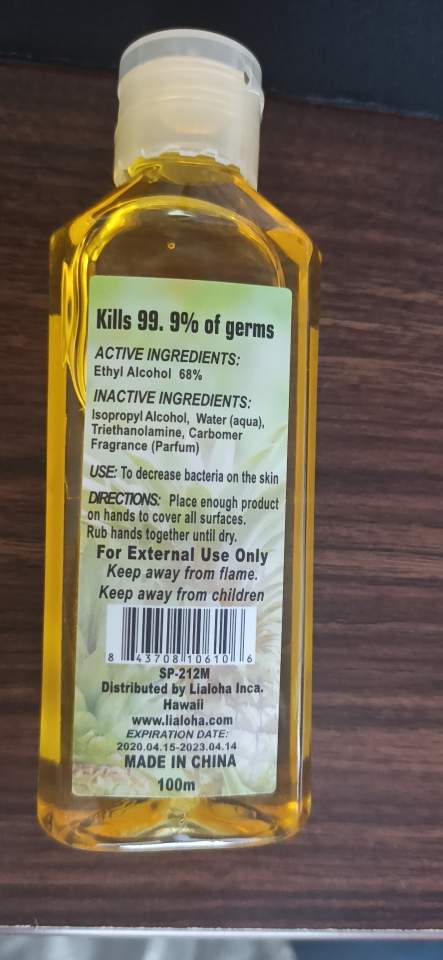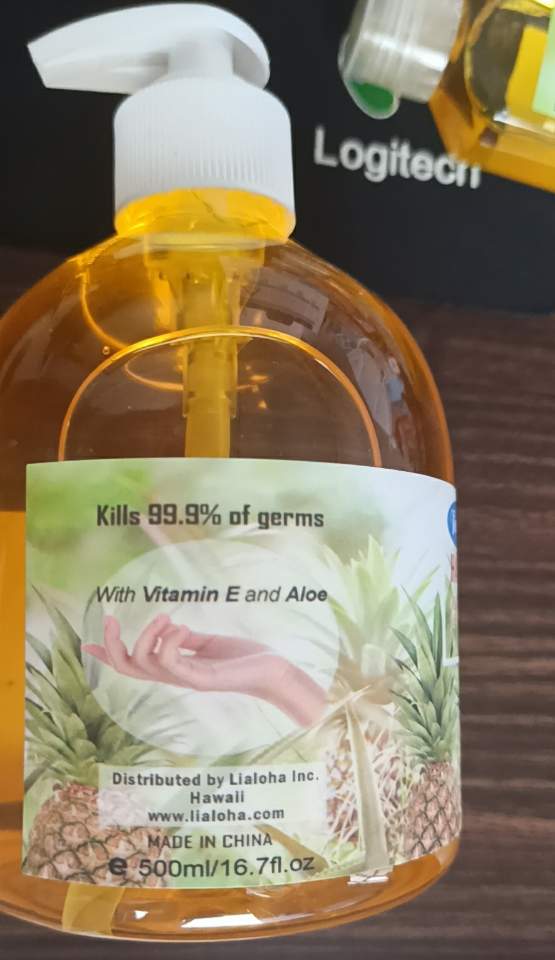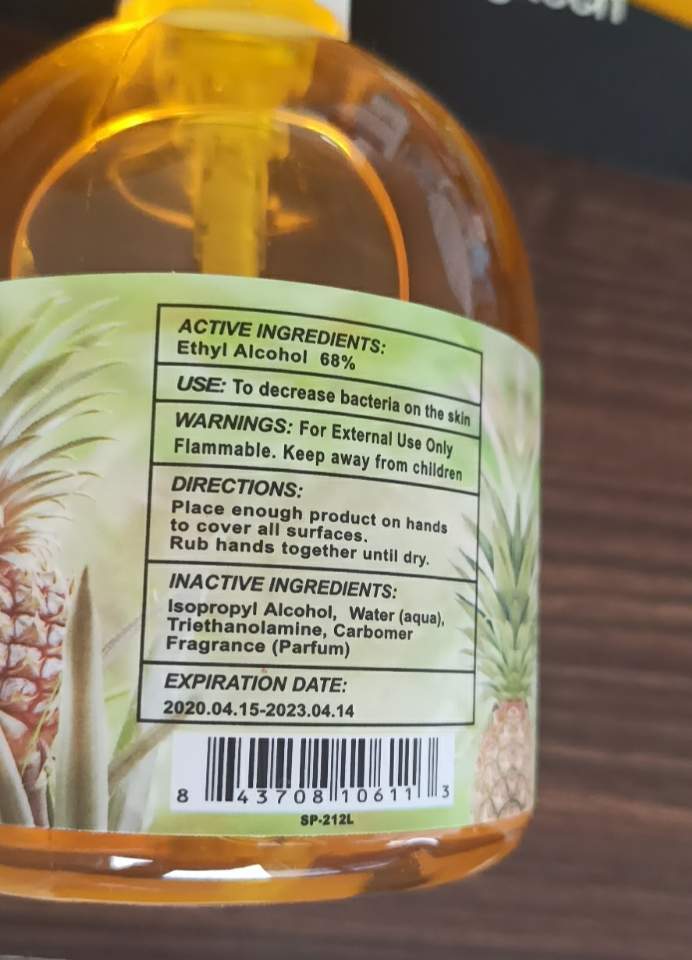 DRUG LABEL: Hand Sanitizer
NDC: 54225-012 | Form: GEL
Manufacturer: Yiwu Sloggi Cosmetics Co.,ltd
Category: otc | Type: HUMAN OTC DRUG LABEL
Date: 20200603

ACTIVE INGREDIENTS: ALCOHOL 68 mL/68 mL
INACTIVE INGREDIENTS: CARBOMER 940; ISOPROPYL ALCOHOL; WATER

54225-012

Active Ingredient(s): Ethyl Alcohol 68%

Purpose

Purpose: Antiseptic

Use

Rub hands together until dry.

Warnings

For external use only.

Do not use

- in children less than 2 months of age
- on open skin wounds

When using this product keep out of eyes, ears, and mouth. In case of contact with eyes, rinse eyes thoroughly with water.
Stop use and ask a doctor if irritation or rash occurs. These may be signs of a serious condition.
Keep out of reach of children. If swallowed, get medical help or contact a Poison Control Center right away.

Stop use and ask a doctor if irritation or rash occurs. These may be signs of a serious condition.

Keep out of reach of children.

Directions

- Place enough product on hands to cover all surfaces.

Other information

- Store between 15-30C (59-86F)
- Avoid freezing and excessive heat above 40C (104F)

Inactive ingredients

Isopropyl Alcohol

Water

Triethanolamine

Carbomer

Fragrance

Package Label - Principal Display Panel

30 mL NDC: 54225-012-01

100 mL NDC: 54225-012-02

500 mL NDC: 54225-012-03